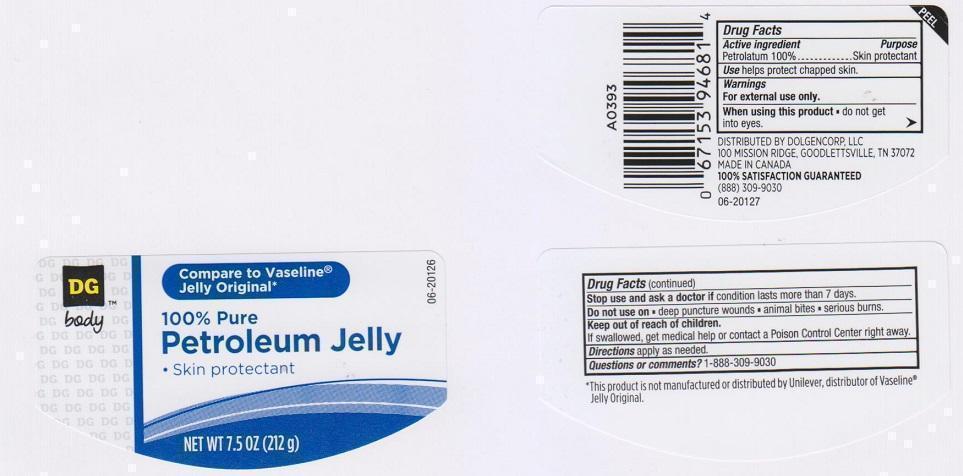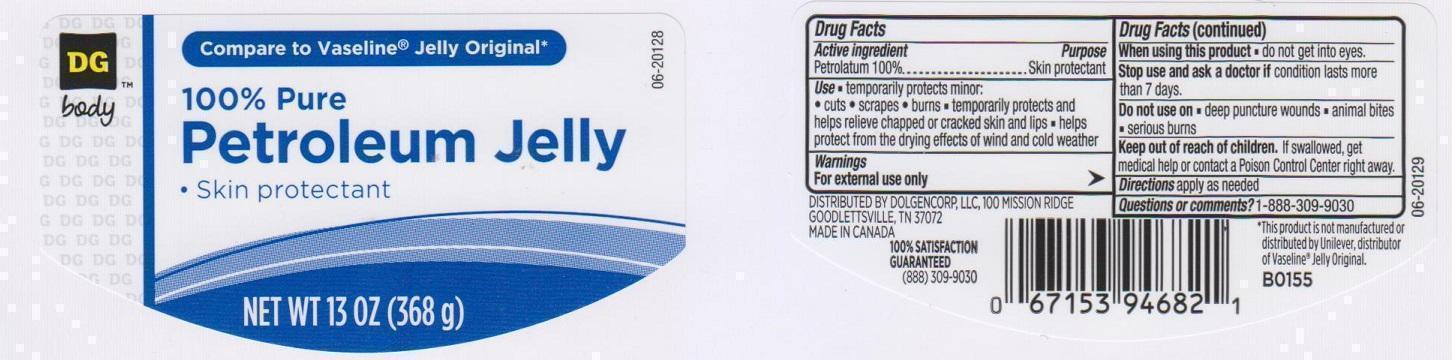 DRUG LABEL: DG BODY
NDC: 55910-350 | Form: JELLY
Manufacturer: DOLGENCORP INC
Category: otc | Type: HUMAN OTC DRUG LABEL
Date: 20150303

ACTIVE INGREDIENTS: PETROLATUM 100 g/100 g

DRUG FACTS

ACTIVE INGREDIENT

PETROLATUM 100%

PURPOSE

SKIN PROTECTANT

USE

- TEMPORARILY PROTECTS MINOR:
- CUTS
- SCRAPES
- BURNS
- TEMPORARILY PROTECTS AND HELPS RELIEVE CHAPPED OR CRACKED SKIN AND LIPS
- HELPS PROTECT FROM THE DRYING EFFECTS OF WIND AND COLD WEATHER

WARNINGS

FOR EXTERNAL USE ONLY

WHEN USING THIS PRODUCT

DOE NOT GET INTO EYES

STOP USE AND ASK A DOCTOR IF

CONDITION LASTS MORE THAN 7 DAYS

DO NOT USE ON

- DEEP PUNCTURE WOUNDS
- ANIMAL BITES
- SERIOUS BURNS

KEEP OUT OF REACH OF CHILDREN

IF SWALLOWED, GET MEDICAL HELP OR CONTACT A POISON CONTROL CENTER RIGHT AWAY

DIRECTIONS

APPLY AS NEEDED

QUESTIONS OR COMMENTS?

1-888-309-9030